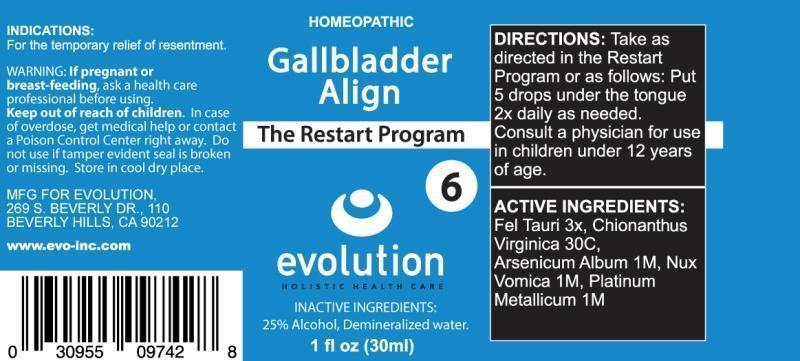 DRUG LABEL: GALLBLADDER ALIGN
NDC: 69414-0002 | Form: LIQUID
Manufacturer: Evolution
Category: homeopathic | Type: HUMAN OTC DRUG LABEL
Date: 20141211

ACTIVE INGREDIENTS: BOS TAURUS BILE 3 [hp_X]/1 mL; CHIONANTHUS VIRGINICUS BARK 30 [hp_C]/1 mL; ARSENIC TRIOXIDE 1 [hp_M]/1 mL; STRYCHNOS NUX-VOMICA SEED 1 [hp_M]/1 mL; PLATINUM 1 [hp_M]/1 mL
INACTIVE INGREDIENTS: WATER; ALCOHOL

DRUG FACTS:

ACTIVE INGREDIENTS:

FEL TAURI 3X, CHIONANTHUS VIRGINICA 30C, ARSENICUM ALBUM 1M, NUX VOMICA 1M, PLATINUM METALLICUM 1M

INDICATIONS:

For the temporary relief of resentment.

WARNINGS:

If pregnant or breast-feeding, ask a health care professional before using.

Keep out of reach of children. In case of overdose, get medical help or contact a Poison Control Center right away.

Do not use if tamper evident seal is broken or missing.

Store in a cool dry place.

Keep out of reach of children. In case of overdose, get medical help or contact a Poison Control Center right away.

DIRECTIONS:

Take as directed in the Restart Program or as follows: Put 5 drops under the tongue 2x daily as needed.

Consult a physician for use in children under 12 years of age.

INDICATIONS:

For the temporary relief of resentment.

INACTIVE INGREDIENTS:

25% Alcohol, Demineralized water.

QUESTIONS:

MFG FOR EVOLUTION,

269 S. BEVERLY DR., 110

BEVERLY HILLS, CA 90212

www.evo-inc.com

PACKAGE LABEL DISPLAY:

HOMEOPATHIC

Gallbladder

Align

The Restart Program

6

evolution

HOLISTIC HEALTH CARE

1 fl oz (30ml)